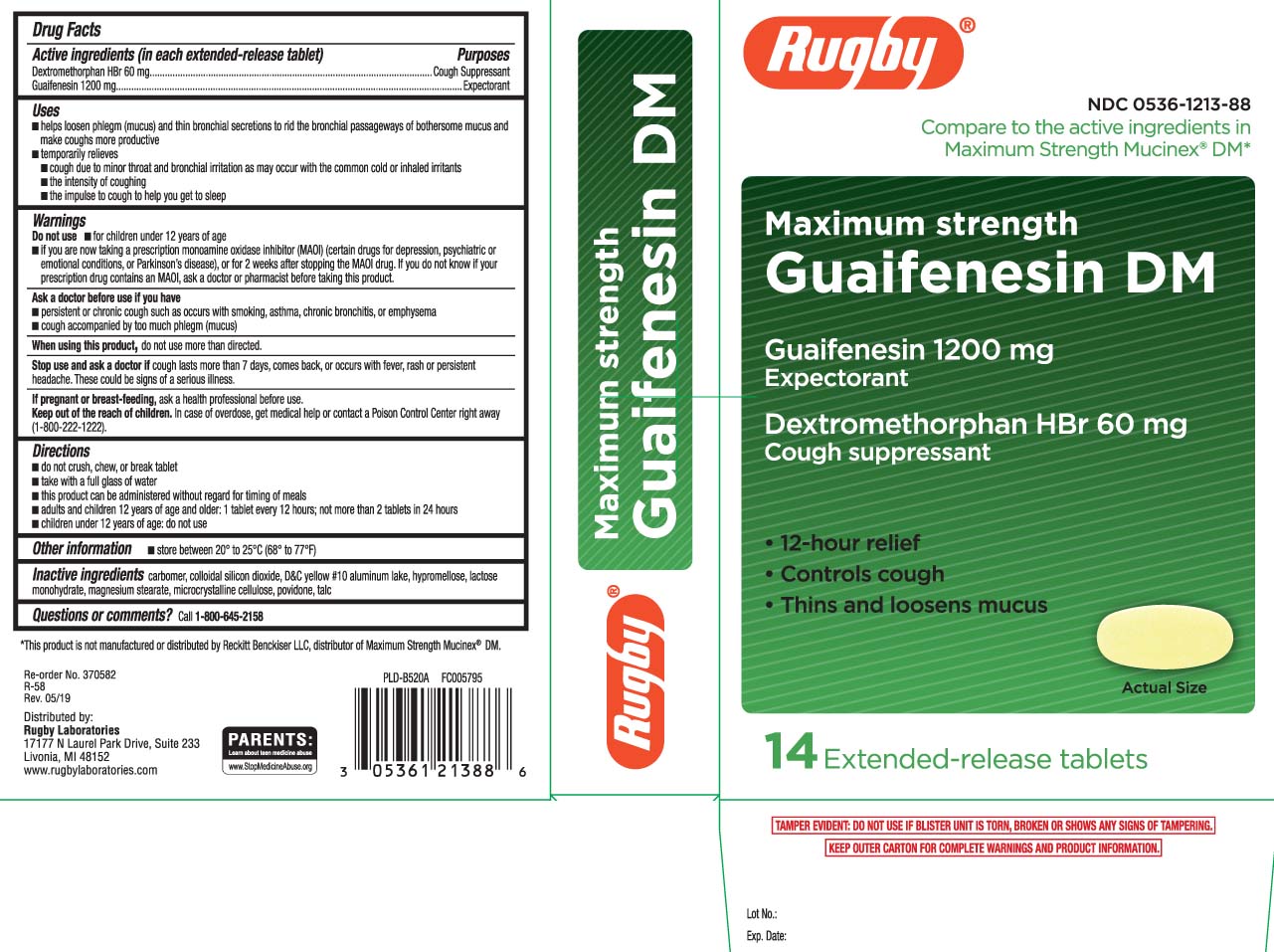 DRUG LABEL: Maximum Strength Guaifenesin DM
NDC: 0536-1213 | Form: TABLET, EXTENDED RELEASE
Manufacturer: Rugby Laboratories
Category: otc | Type: HUMAN OTC DRUG LABEL
Date: 20260210

ACTIVE INGREDIENTS: DEXTROMETHORPHAN HYDROBROMIDE 60 mg/1 1; GUAIFENESIN 1200 mg/1 1
INACTIVE INGREDIENTS: CARBOMER 934; SILICON DIOXIDE; D&C YELLOW NO. 10; HYPROMELLOSE, UNSPECIFIED; LACTOSE MONOHYDRATE; MAGNESIUM STEARATE; CELLULOSE, MICROCRYSTALLINE; POVIDONE; TALC

Drug Facts

Active ingredients (in each extended-release tablet)

Dextromethorphan HBr 60 mg

Guaifenesin 1200 mg

Purpose

Cough Suppressant

Expectorant

Uses

- helps loosen phlegm (mucus) and thin bronchial secretions to rid the bronchial passageways of bothersome mucus and make coughs more productive
- temporarily relieves
  - cough due to minor throat and bronchial irritation as may occur with the common cold or inhaled irritants
  - the intensity of coughing
  - the impulse to cough to help you get to sleep

Warnings

Do not use

- for children under12 years of age
- if you are now taking a prescription monoamine oxidase inhibitor (MAOI) (certain drugs for depression, psychiatric or emotional conditions, or Parkinson's disease), or for 2 weeks after stopping the MAOI drug. If you do not know if your prescription drug contains an MAOI, ask a doctor or pharmacist before taking this product.

Ask a doctor before use if you have

- persistent or chronic cough such as occurs with smoking, asthma, chronic bronchitis, or emphysema
- cough accompanied by too much phlegm (mucus)

When using this product,

do not use more than directed.

Stop use and ask a doctor if

cough lasts more than 7 days, comes back, or occurs with fever, rash or persistent headache. These could be signs of a serious illness.

If pregnant or breast-feeding,

ask a health professional before use.

Keep out of reach of children.

In case of overdose, get medical help or contact a Poison Control Center right away (1-800-222-1222).

Directions

- do not crush, chew, or break tablet
- take with a full glass of water
- this product can be administered without regards for timing of meals
- adults and children 12 years of age and older: 1 tablet every 12 hours; not more than 2 tablets in 24 hours
- children under 12 years of age: do not use

Other information

- store between 20º to 25ºC (68º to 77ºF)

Inactive ingredients

carbomer, colloidal silicon dioxide, D&Cyellow #10 aluminum lake, hypromellose, lactose monohydrate, magnesium stearate, microcrystalline cellulose, povidone, talc

Questions or comments?

Call 1-877-753-3935 Monday-Friday 9AM-5PM EST

Principal Display Panel

Compare to the active ingredients in Maximum Strength Mucinex® DM*

Maximum strength

Mucus Relief DM

Guaifenesin | 1200 mg

Expectorant

Dextromethorphan HBr | 60 mg

Cough Suppressant

- 12-hour relief
- Controls Cough
- Thins & Loosens Mucus

Extended Release Tablets

*This product is not manufactured or distributed Reckitt Benckiser LLC, distributor of Maximum Strength Mucinex® DM.

TAMPER EVIDENT: DO NOT USE IF BLISTER UNIT IS TORN, BROKEN OR SHOWS ANY SIGNS OF TAMPERING.

KEEP OUTER CARTON FOR COMPLETE WARNINGS AND PRODUCT INFORMATION.

Distributed by:

Rugby Laboratories

17177 N Laurel Park Drive, Suite 233

Livonia, MI 48152

www.rugbylaboratories.com

Package Label

RUGBY Maximum Strength Guaifenesin DM